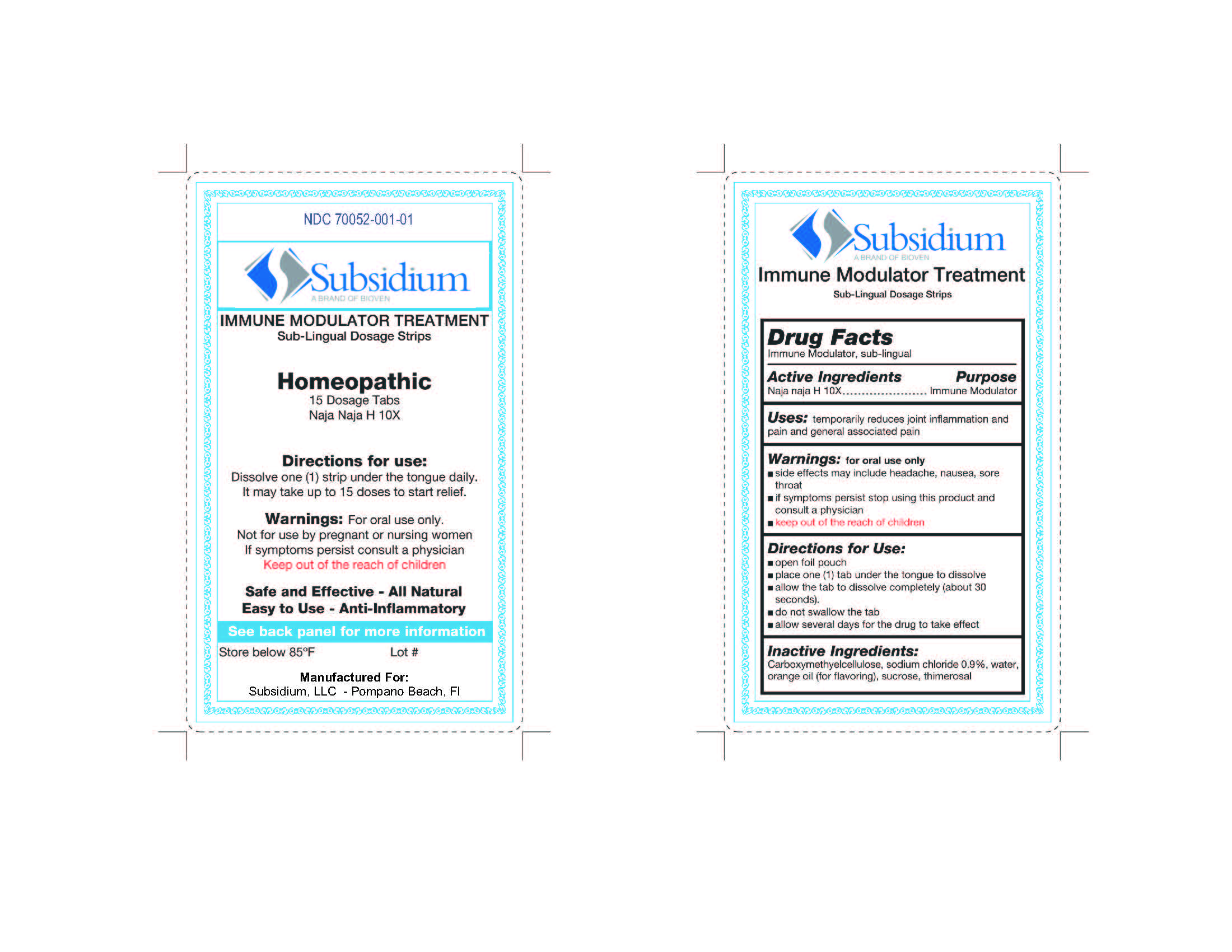 DRUG LABEL: Subsidium
NDC: 70052-001 | Form: STRIP
Manufacturer: Subsidium, LLC
Category: homeopathic | Type: HUMAN OTC DRUG LABEL
Date: 20160127

ACTIVE INGREDIENTS: NAJA NAJA VENOM 10 [hp_X]/1 1
INACTIVE INGREDIENTS: SODIUM CHLORIDE; CARBOXYMETHYLCELLULOSE; WATER; SUCROSE; THIMEROSAL; ORANGE OIL

WARNINGS

For oral use only

If symptoms persist stop using this product and consult a physician

Side effects may include headache, nausea, sore throat

Directions for use

Dissolve one (1) strip under the tongue daily. It may take up to 15 doses to start relief.

Keep out of reach of children

ACTIVE INGREDIENT

Naja Naja H 10X

INACTIVE INGREDIENT

Carboxymethyelcellulose, sodium chloride 0.9%, water, natural orange flavorings, sucrose , thimerosol

PURPOSE

Immune Modulator

PREGNANCY OR BREAST FEEDING

Not for use by pregnant or nursing women

Uses

Temporarily reduces joint inflammation and pain and general associated pain.